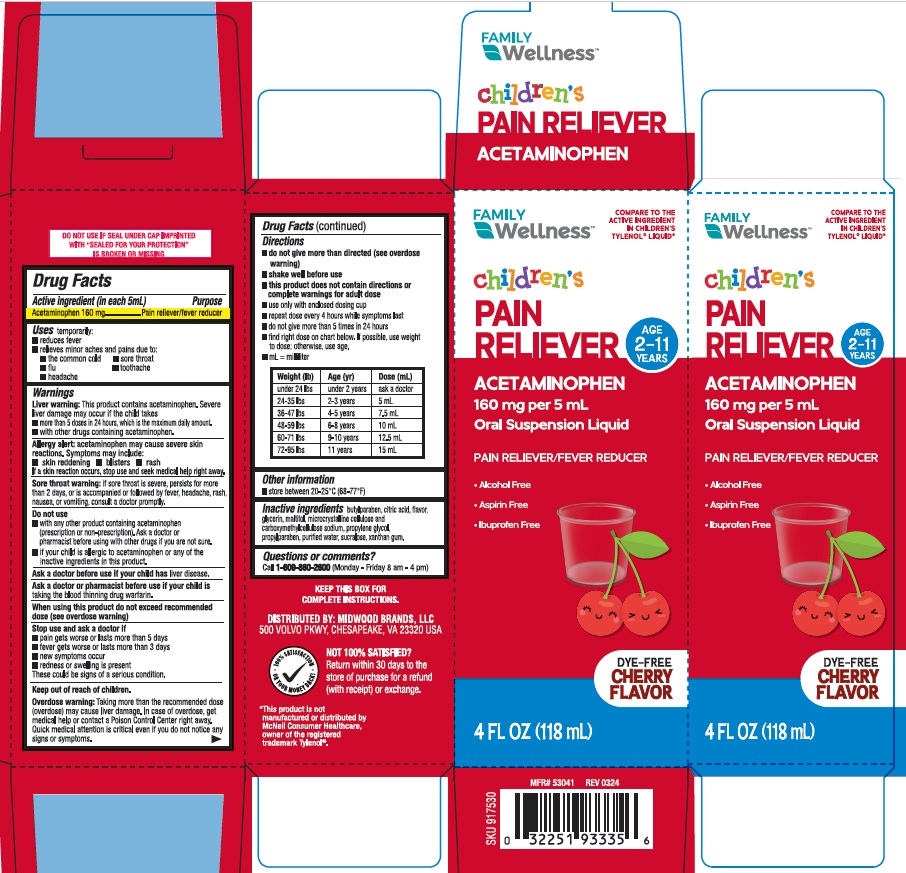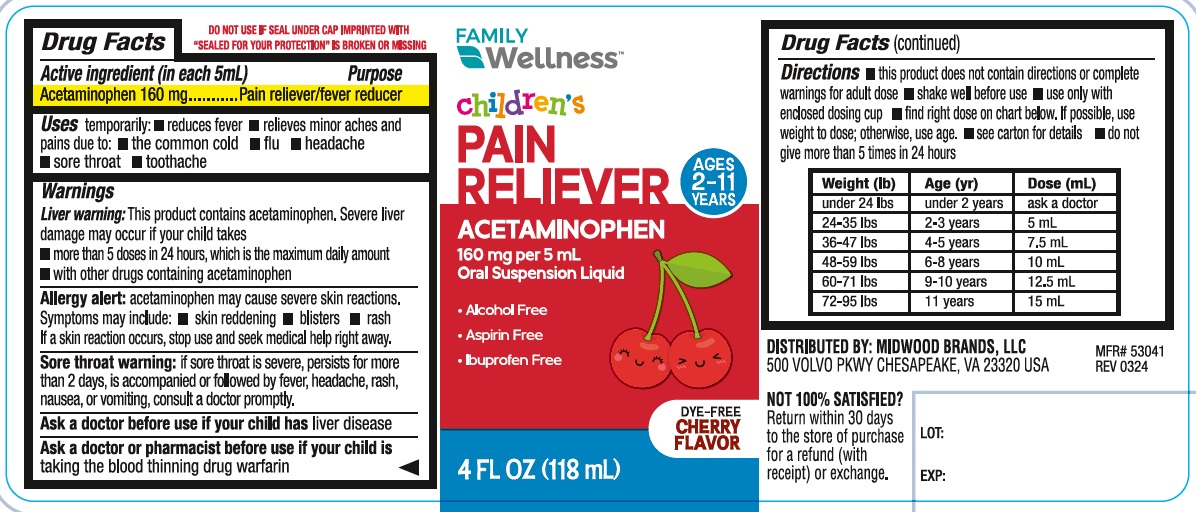 DRUG LABEL: Family Wellness Childrens Pain Reliever 574
NDC: 55319-930 | Form: SUSPENSION
Manufacturer: Family Dollar Services, Inc.
Category: otc | Type: Human OTC Drug Label
Date: 20251201

ACTIVE INGREDIENTS: ACETAMINOPHEN 160 mg/5 mL
INACTIVE INGREDIENTS: BUTYLPARABEN; ANHYDROUS CITRIC ACID; GLYCERIN; MALTITOL; MICROCRYSTALLINE CELLULOSE; CARBOXYMETHYLCELLULOSE SODIUM, UNSPECIFIED; PROPYLENE GLYCOL; PROPYLPARABEN; SUCRALOSE; XANTHAN GUM; WATER

Family Wellness Childrens Pain reliever 574

ACTIVE INGREDIENT(S)

Acetaminophen 160mg

PURPOSE

Pain reliever/fever reducer

USE(S)

temporarily:

- reduces fever
- relieves minor aches and pains due to:
  - the common cold
  - sore throat
  - flu
  - toothache
  - headache

WARNINGS

Liver warning: This product contains acetaminophen. Severe liver damage may occur if the child takes

- more than 5 doses in 24 hours, which is the maximum daily amount.
- with other drugs containing acetaminophen.

Allergy alert: acetaminophen may cause severe skin reactions. Symptoms may include:

- skin reddening
- blisters
- rash

If a skin reaction occurs, stop use and seek medical help right away.

Sore throat warning: if sore throat is severe, persists for more than 2 days, or is accompanied or followed by fever, headache, rash, nausea, or vomiting, consult a doctor promptly.

DO NOT USE

- with any other product containing acetaminophen (prescription or non-prescription). Ask a doctor or pharmacist before using with other drugs if you are not sure.
- if your child is allergic to acetaminophen or any of the inactive ingredients in this product.

ASK A DOCTOR BEFORE USE IF YOUR CHILD HAS

liver disease.

ASK A DOCTOR OR PHARMACIST BEFORE USE IF YOUR CHILD IS

taking the blood thinning drug warfarin.

WHEN USING THIS PRODUCT

do not exceed recommended dose (see overdose warning)

STOP USE AND ASK DOCTOR IF

- pain gets worse or last more than 5 days
- fever gets worse or lasts more than 3 days
- new symptoms occur
- redness or swelling is present

These could be signs of a serious condition.

KEEP OUT OF REACH OF CHILDREN

Overdose warning: Taking more than the recommended dose (overdose) may cause liver damage. In case of overdose, get medical help or contact a Poison Control Center right away. Quick medical attention is critical even if you do not notice any signs or symptoms.

DIRECTIONS

- do not give more than directed (see overdose warning)
- shake well before use
- this product does not contain directions or complete warning for adult dose
- use only with enclosed dosing cup
- repeat dose every 4 hours while symptoms last
- find right dose on chart below. If possible, use weight to dose; otherwise, use age.
- mL = milliliter

Weight (lb) | Age (yr) | Dose (mL)
under 24 lbs | under 2 years | ask a doctor
24-35 lbs | 2-3 years | 5 mL
36-47 lbs | 4-5 years | 7.5 mL
48-59 lbs | 6-8 years | 10 mL
60-71 lbs | 9-10 years | 12.5 mL
72-95 lbs | 11 years | 15 mL

OTHER INFORMATION

store between 20-25ºC (68-77ºF)

INACTIVE INGREDIENTS

butylparaben, citric acid, flavor, glycerin, maltitol, microcrystalline cellulose and carboxymethylcellulose sodium, propylene glycol, propylparaben, purified water, sucralose, Xanthan gum.

QUESTIONS OR COMMENTS?

Call 1-609-860-2600 (Monday - Friday 8 am - 4 pm)

PRINCIPAL DISPLAY PANEL

FAMILY WellnessTM

COMPARE TO THE ACTIVE INGREDIENT IN CHILDRENS TYLENOL® LIQUID*

children's PAIN RELIEVEER

AGE 2 - 11 YEARS

ACETAMINOPHEN 160 mg per 5 mL

Oral Suspension Liquid

PAIN RELIEVER/FEVER REDUCER

- Alcohol Free
- Aspirin Free
- Ibuprofen Free

DYE-FREE

CHERRY FLAVOR

4 FL OZ (118 mL)